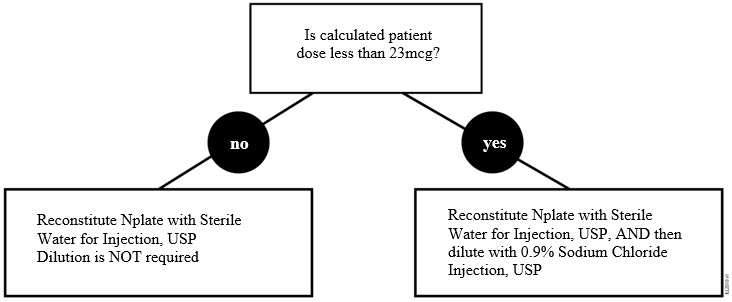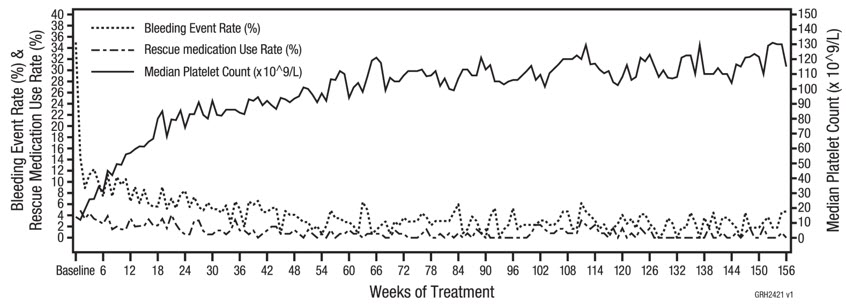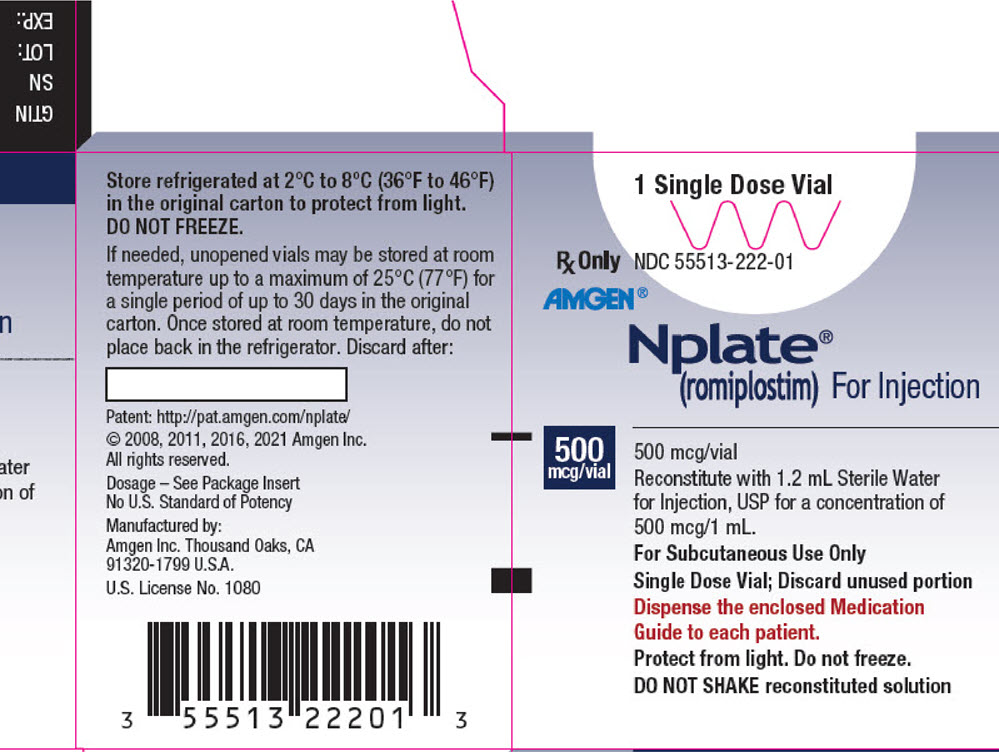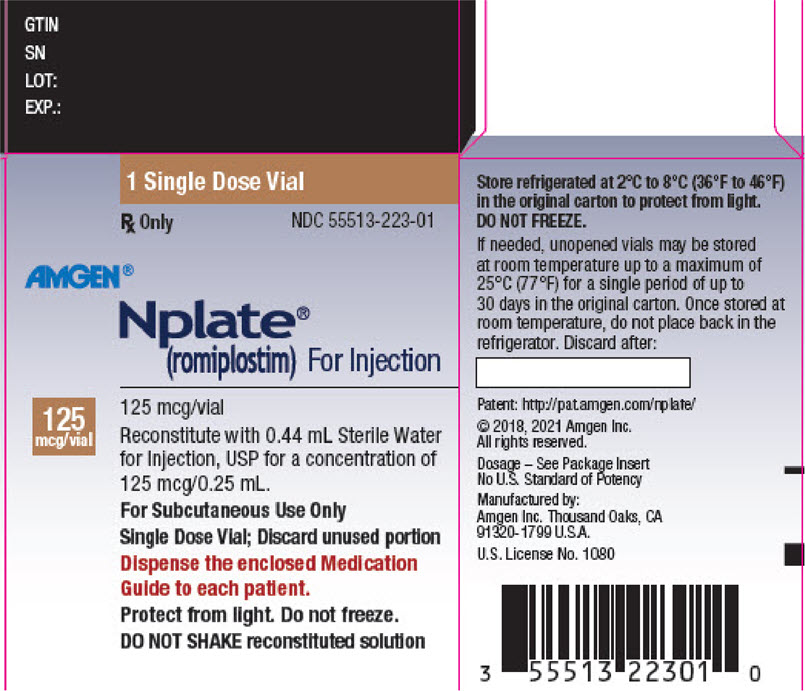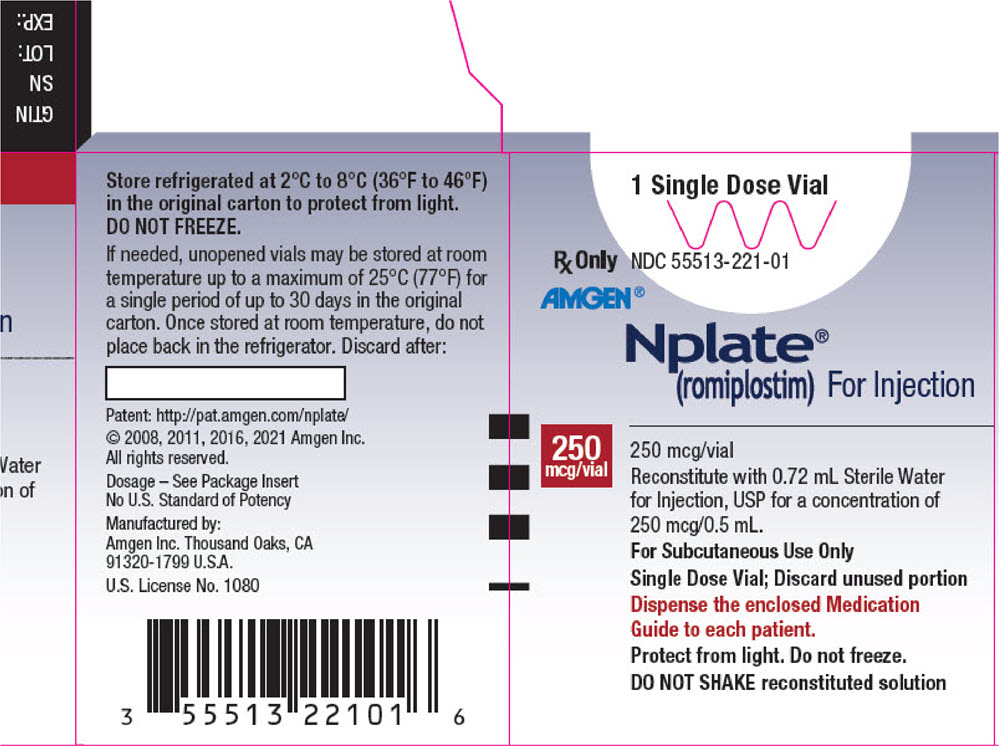 DRUG LABEL: Nplate
NDC: 55513-222 | Form: INJECTION, POWDER, LYOPHILIZED, FOR SOLUTION
Manufacturer: Amgen, Inc
Category: prescription | Type: HUMAN PRESCRIPTION DRUG LABEL
Date: 20250313

ACTIVE INGREDIENTS: ROMIPLOSTIM 500 ug/1 mL
INACTIVE INGREDIENTS: HYDROCHLORIC ACID; HISTIDINE 10 mmol/1 mL; MANNITOL 40 mg/1 mL; POLYSORBATE 20 0.04 mg/1 mL; SUCROSE 20 mg/1 mL

HIGHLIGHTS OF PRESCRIBING INFORMATION

These highlights do not include all the information needed to use NPLATE safely and effectively. See full prescribing information for NPLATE.
NPLATE® (romiplostim) for injection, for subcutaneous use
Initial U.S. Approval: 2008

RECENT MAJOR CHANGES

Warnings and Precautions, Thrombotic/Thromboembolic Complications (5.2) | 02/2025
Warnings and Precautions, Loss of Response to Nplate (5.3) | 02/2025

1 INDICATIONS AND USAGE

Nplate is a thrombopoietin receptor agonist indicated for the treatment of thrombocytopenia in:

- Adult patients with immune thrombocytopenia (ITP) who have had an insufficient response to corticosteroids, immunoglobulins, or splenectomy. (1.1)
- Pediatric patients 1 year of age and older with ITP for at least 6 months who have had an insufficient response to corticosteroids, immunoglobulins, or splenectomy. (1.1)

Nplate is indicated to increase survival in adults and in pediatric patients (including term neonates) acutely exposed to myelosuppressive doses of radiation (Hematopoietic Syndrome of Acute Radiation Syndrome [HS-ARS]). (1.2)

Limitations of Use:

- Nplate is not indicated for the treatment of thrombocytopenia due to myelodysplastic syndrome (MDS) or any cause of thrombocytopenia other than ITP.
- Nplate should be used only in patients with ITP whose degree of thrombocytopenia and clinical condition increases the risk for bleeding.
- Nplate should not be used in an attempt to normalize platelet counts. (1)

2 DOSAGE AND ADMINISTRATION

- Patients with Immune Thrombocytopenia (ITP)
  - Recommended Initial Dose: 1 mcg/kg once weekly as a subcutaneous injection. Adjust dose based on platelet response. (2.1)
- Patients acutely exposed to myelosuppressive doses of radiation
  - Recommended Dose: 10 mcg/kg administered once as a subcutaneous injection. Administer the dose as soon as possible after suspected or confirmed exposure to myelosuppressive doses of radiation. (2.2)
- See Full Prescribing Information for instructions on reconstitution, preparation, and administration. (2.3)

3 DOSAGE FORMS AND STRENGTHS

- For injection: 125 mcg, 250 mcg or 500 mcg of romiplostim as a lyophilized powder in single-dose vials. (3)

4 CONTRAINDICATIONS

None (4)

5 WARNINGS AND PRECAUTIONS

- In some patients with MDS, Nplate increases blast cell counts and increases the risk of progression to acute myelogenous leukemia. (5.1)
- Thrombotic/thromboembolic complications have resulted from increases in platelet counts with Nplate use. Portal vein thrombosis has been reported in patients with chronic liver disease receiving Nplate. (5.2)
- Severe thrombocytopenia may persist during Nplate treatment due to neutralizing antibodies or other causes. (5.3)

6 ADVERSE REACTIONS

- In adult patients, the most common adverse reactions (≥ 5% higher patient incidence in Nplate versus placebo) are arthralgia, dizziness, insomnia, myalgia, pain in extremity, abdominal pain, shoulder pain, dyspepsia, and paresthesia. Headache was the most commonly reported adverse reaction that did not occur at ≥ 5% higher patient incidence in Nplate versus placebo. (6.1)
- In pediatric patients, the most common adverse reactions (≥ 25%) are: contusion, upper respiratory tract infection, and oropharyngeal pain. (6.1)

To report SUSPECTED ADVERSE REACTIONS, contact Amgen Inc. at 1-800-77-AMGEN (1-800-772-6436) or FDA at 1-800-FDA-1088 or www.fda.gov/medwatch.

8 USE IN SPECIFIC POPULATIONS

- Pregnancy: May cause fetal harm. (8.1)
- Lactation: Advise not to breastfeed. (8.2)

FULL PRESCRIBING INFORMATION

1 INDICATIONS AND USAGE

1.1 Patients with Immune Thrombocytopenia (ITP)

Nplate is indicated for the treatment of thrombocytopenia in:

- Adult patients with immune thrombocytopenia (ITP) who have had an insufficient response to corticosteroids, immunoglobulins, or splenectomy.
- Pediatric patients 1 year of age and older with ITP for at least 6 months who have had an insufficient response to corticosteroids, immunoglobulins, or splenectomy.

1.2 Patients with Hematopoietic Syndrome of Acute Radiation Syndrome

Nplate is indicated to increase survival in adults and in pediatric patients (including term neonates) acutely exposed to myelosuppressive doses of radiation [see Clinical Studies (14.3)].

Limitations of Use:

- Nplate is not indicated for the treatment of thrombocytopenia due to myelodysplastic syndrome (MDS) or any cause of thrombocytopenia other than ITP [see Warnings and Precautions (5.1)].
- Nplate should be used only in patients with ITP whose degree of thrombocytopenia and clinical condition increases the risk for bleeding.
- Nplate should not be used in an attempt to normalize platelet counts [see Warnings and Precautions (5.2)].

2 DOSAGE AND ADMINISTRATION

2.1 Patients with Immune Thrombocytopenia (ITP)

Use the lowest dose of Nplate to achieve and maintain a platelet count ≥ 50 × 10^9/L as necessary to reduce the risk for bleeding. Administer Nplate as a weekly subcutaneous injection with dose adjustments based upon the platelet count response.

The prescribed Nplate dose may consist of a very small volume (e.g., 0.15 mL). Administer Nplate only with a syringe that contains 0.01 mL graduations.

Discontinue Nplate if the platelet count does not increase to a level sufficient to avoid clinically important bleeding after 4 weeks of Nplate therapy at the maximum weekly dose of 10 mcg/kg [see Warnings and Precautions (5.3)].

Obtain complete blood counts (CBCs), including platelet counts, weekly during the dose adjustment phase of Nplate therapy and then monthly following establishment of a stable Nplate dose. Obtain CBCs, including platelet counts, weekly for at least 2 weeks following discontinuation of Nplate.

For Adult Patients with ITP

The initial dose of Nplate is 1 mcg/kg. Actual body weight at initiation of treatment should always be used when calculating the initial dose. In adults, future dose adjustments are based on changes in platelet counts only.

Adjust the weekly dose of Nplate by increments of 1 mcg/kg until the patient achieves a platelet count ≥ 50 × 10^9/L as necessary to reduce the risk for bleeding; do not exceed a maximum weekly dose of 10 mcg/kg. In clinical studies, most adult patients who responded to Nplate achieved and maintained platelet counts ≥ 50 × 10^9/L with a median dose of 2-3 mcg/kg.

Adjust the dose as follows for adult patients:

- If the platelet count is < 50 × 10^9/L, increase the dose by 1 mcg/kg.
- If platelet count is > 200 × 10^9/L and ≤ 400 × 10^9/L for 2 consecutive weeks, reduce the dose by 1 mcg/kg.
- If platelet count is > 400 × 10^9/L, do not dose. Continue to assess the platelet count weekly. After the platelet count has fallen to < 200 × 10^9/L, resume Nplate at a dose reduced by 1 mcg/kg.

For Pediatric Patients with ITP

The initial dose of Nplate is 1 mcg/kg. Actual body weight at initiation of treatment should always be used when calculating initial dose. In pediatric patients, future dose adjustments are based on changes in platelet counts and changes in body weight. Reassessment of body weight is recommended every 12 weeks.

Adjust the weekly dose of Nplate by increments of 1 mcg/kg until the patient achieves a platelet count ≥ 50 × 10^9/L as necessary to reduce the risk for bleeding; do not exceed a maximum weekly dose of 10 mcg/kg. In a pediatric placebo-controlled clinical study, the median of the most frequent dose of Nplate received by patients during weeks 17 through 24 was 5.5 mcg/kg.

Adjust the dose as follows for pediatric patients:

- If the platelet count is < 50 × 10^9/L, increase the dose by 1 mcg/kg.
- If platelet count is > 200 × 10^9/L and ≤ 400 × 10^9/L for 2 consecutive weeks, reduce the dose by 1 mcg/kg.
- If platelet count is > 400 × 10^9/L, do not dose. Continue to assess the platelet count weekly. After the platelet count has fallen to < 200 × 10^9/L, resume Nplate at a dose reduced by 1 mcg/kg.

2.2 Patients with Hematopoietic Syndrome of Acute Radiation Syndrome

For Adult and Pediatric Patients (including term neonates)

The recommended dose of Nplate is 10 mcg/kg administered once as a subcutaneous injection. Administer the dose as soon as possible after suspected or confirmed exposure to radiation levels greater than 2 gray (Gy).

Administer Nplate regardless of whether a complete blood count (CBC) can be obtained. Estimate a patient's absorbed whole body radiation dose (i.e., level of radiation exposure) based on information from public health authorities, biodosimetry if available, or clinical findings such as time to onset of vomiting or lymphocyte depletion kinetics.

2.3 Preparation and Administration

To mitigate against medication errors (both overdose and underdose), ensure that these preparation and administration instructions are followed. Use aseptic technique. Only administer subcutaneously [see Overdosage (10)].

Nplate is supplied in single-dose vials as a sterile, preservative-free, white lyophilized powder that must be reconstituted as outlined in Table 1 and administered using a syringe with 0.01 mL graduations.

Calculation of Patient Dose

Multiply the patient’s weight (kg) by the prescribed dose to obtain the Calculated Patient Dose.

Calculated Patient Dose (mcg) = Weight (kg) × Prescribed dose (mcg/kg)

Reconstitution and Dilution of Nplate Single-Dose Vials

Reconstitute Nplate with Sterile Water for Injection, USP. Do not reconstitute or dilute with Bacteriostatic Water for Injection, USP or dilute with Bacteriostatic Sodium Chloride Injection, USP. If the Calculated Patient Dose is less than 23 mcg, dilution with 0.9% Sodium Chloride Injection, USP is required to reduce the concentration of Nplate (see Table 1). This reduced concentration allows for low-doses to be accurately calculated, and consistently measured with a 0.01 mL graduated syringe.

Table 1. Reconstitution and Dilution of Nplate Single-Dose Vials
Calculated Patient Dose | Strength [Vial contains overfill to ensure delivery of labeled vial strength.] | Reconstitute with Sterile Water [Add Sterile Water for Injection, USP directly to the vial.] | Dilute with Normal Saline [Add 0.9% Sodium Chloride Injection, USP directly to the vial.] | Final Concentration
Calculated Dose greater than or equal to 23 mcg | 125 mcg | 0.44 mL | Not Required | 500 mcg/mL
Calculated Dose greater than or equal to 23 mcg | 250 mcg | 0.72 mL | Not Required
Calculated Dose greater than or equal to 23 mcg | 500 mcg | 1.2 mL | Not Required
Calculated Dose less than 23 mcg | 125 mcg | 0.44 mL | 1.38 mL | 125 mcg/mL
Calculated Dose less than 23 mcg | 250 mcg | 0.72 mL | 2.25 mL
Calculated Dose less than 23 mcg | 500 mcg | 1.2 mL | 3.75 mL

Gently swirl and invert the vial to reconstitute. Avoid excess or vigorous agitation: DO NOT SHAKE. Generally, dissolution of Nplate takes less than 2 minutes. The reconstituted Nplate solution should be clear and colorless. Visually inspect the reconstituted solution for particulate matter and/or discoloration. Do not administer Nplate if particulate matter and/or discoloration is observed.

Calculate Volume to Administer by dividing the Calculated Patient Dose (mcg) by the final concentration of prepared solution. See Table 2 for final concentrations.

Table 2. Administration of Prepared Nplate Solution
Calculated Patient Dose | Final Concentration | Volume to Administer (mL)
Calculated Dose greater than or equal to 23 mcg | 500 mcg/mL | = Calculated Patient Dose / 500 mcg/mL
Calculated Dose less than 23 mcg | 125 mcg/mL | = Calculated Patient Dose / 125 mcg/mL

Administration of Prepared Nplate Solution

Administer Nplate only using a syringe with 0.01 mL graduations for accurate dosage. Round volume to the nearest hundredth mL. Verify that the syringe contains the correct dosage.

Discard any unused portion. Do not pool unused portions from the vials. Do not administer more than one dose from a vial.

Storage of Reconstituted Solution

Reconstituted product with Sterile Water for Injection, USP that has not been further diluted can remain in the original vial at room temperature 25°C (77°F) or be refrigerated at 2°C to 8°C (36°F to 46°F) for up to 24 hours following reconstitution. Reconstituted product with Sterile Water for Injection, USP may be held in a syringe at room temperature 25°C (77°F) for a maximum of 4 hours following reconstitution. Protect product from light. Do not shake.

Storage of Diluted solution (after initial reconstitution)

Reconstituted and further diluted product with 0.9% Sodium Chloride Injection, USP can be held in a syringe at room temperature 25°C (77°F) or in the original vial refrigerated at 2°C to 8°C (36°F to 46°F) for no longer than 4 hours prior to administration. Protect product from light. Do not shake.

3 DOSAGE FORMS AND STRENGTHS

For injection: 125 mcg, 250 mcg or 500 mcg of Nplate as a sterile, lyophilized, solid white powder in single-dose vials.

4 CONTRAINDICATIONS

None.

5 WARNINGS AND PRECAUTIONS

5.1 Risk of Progression of Myelodysplastic Syndromes to Acute Myelogenous Leukemia

Progression from myelodysplastic syndromes (MDS) to acute myelogenous leukemia (AML) has been observed in adult clinical trials with Nplate.

A randomized, double-blind, placebo-controlled trial enrolling adult patients with severe thrombocytopenia and International Prognostic Scoring System (IPSS) low or intermediate-1 risk MDS was terminated due to more cases of AML observed in the Nplate arm. This trial consisted of a 58-week study period with a 5-year long-term follow-up phase. The patients were randomized 2:1 to treatment with Nplate or placebo (167 Nplate, 83 placebo). During the 58-week study period, progression to AML occurred in 10 (6.0%) patients in the Nplate arm and 4 (4.8%) patients in the placebo arm (hazard ratio [95%CI] = 1.20 [0.38, 3.84]). Of the 250 patients, 210 (84.0%) entered the long-term follow-up phase of this study. With 5 years of follow-up, 29 (11.6%) patients showed progression to AML, including 20/168 (11.9%) patients in the Nplate arm versus 9/82 (11.0%) patients in the placebo arm (HR [95% CI] = 1.06 [0.48, 2.33]). The incidence of death (overall survival) was 55.7% (93/167) in the Nplate arm versus 54.2% (45/83) in the placebo arm (HR [95% CI] = 1.03 [0.72, 1.47]). In the baseline low IPSS group, there was a higher incidence of death in the Nplate arm [41.3% (19/46)] compared to the placebo arm [30.4% (7/23)] (HR [95% CI] = 1.59 [0.67, 3.80]).

In a single-arm trial of Nplate given to 72 patients with thrombocytopenia-related MDS, 8 (11.1%) patients were reported as having possible disease progression, of which 3 (4.2%) had confirmation of AML during follow-up. In addition, in 3 (4.2%) patients, increased peripheral blood blast cell counts decreased to baseline after discontinuation of Nplate.

Nplate is not indicated for the treatment of thrombocytopenia due to MDS or any cause of thrombocytopenia other than ITP.

5.2 Thrombotic/Thromboembolic Complications

Thrombotic/thromboembolic complications have resulted from increases in platelet counts with Nplate use secondary to drug-induced thrombocytosis, regardless of the underlying disease. Thrombotic/ thromboembolic events including deep vein thrombosis (1.4%), pulmonary embolism (1.2%) and myocardial infarction (0.8%) have been observed with the use of Nplate in the ITP population. Other thrombotic events including transient ischemic attack have been reported. These events have occurred regardless of platelet counts. Portal vein thrombosis has been reported in patients with and without chronic liver disease receiving Nplate.

In patients with ITP, to minimize the risk for thrombotic/thromboembolic complications, do not use Nplate in an attempt to normalize platelet counts. Follow the dose adjustment guidelines [see Dosage and Administration (2.1)].

In the absence of myelosuppression induced by acute exposure to radiation, Nplate administration might cause excessive increases in platelet counts and may cause thrombotic and thromboembolic complications [see Clinical Pharmacology (12.2)].

5.3 Loss of Response to Nplate

Hyporesponsiveness or failure to maintain a platelet response with Nplate may occur due to neutralizing antibodies or other causes [see Adverse Reactions (6.3)]. Discontinue Nplate if the platelet count does not increase to a level sufficient to avoid clinically important bleeding after 4 weeks at the highest weekly dose of 10 mcg/kg.

6 ADVERSE REACTIONS

The following clinically significant adverse reactions are discussed in greater detail in other sections:

- Progression of Myelodysplastic Syndromes [see Warnings and Precautions (5.1)]
- Thrombotic/Thromboembolic Complications [see Warnings and Precautions (5.2)]
- Loss of Response to Nplate [see Warnings and Precautions (5.3)]

6.1 Clinical Trials Experience

Because clinical trials are conducted under widely varying conditions, adverse reaction rates observed in the clinical trials of a drug cannot be directly compared to rates in the clinical trials of another drug and may not reflect the rates observed in practice.

Adults

The data described below reflect Nplate exposure to 271 adult patients with ITP, aged 18 to 88, of whom 62% were female. Nplate was studied in two randomized, placebo-controlled, double-blind studies that were identical in design, with the exception that Study 1 evaluated non-splenectomized patients with ITP and Study 2 evaluated splenectomized patients with ITP. Data are also reported from an open-label, single-arm study in which patients received Nplate over an extended period of time. Overall, Nplate was administered to 114 patients for at least 52 weeks and 53 patients for at least 96 weeks.

In the placebo-controlled studies, headache was the most commonly reported adverse drug reaction, occurring in 35% of patients receiving Nplate and 32% of patients receiving placebo. For those patients receiving Nplate, 14 (48%) of headaches were mild, 9 (31%) were moderate, and 6 (21%) were severe. Table 3 presents adverse drug reactions from Studies 1 and 2 with a ≥ 5% higher patient incidence in Nplate versus placebo.

Table 3. Adverse Reactions Identified in Two Placebo-Controlled Studies
Adverse Reactions by Body System | Nplate (%) (n=84) | Placebo (%) (n=41)
Musculoskeletal and Connective Tissue Disorders
Arthralgia | 22 (26%) | 8 (20%)
Myalgia | 12 (14%) | 1 (2%)
Pain in Extremity | 11 (13%) | 2 (5%)
Shoulder Pain | 7 (8%) | 0
Nervous System Disorders
Dizziness | 14 (17%) | 0
Paresthesia | 5 (6%) | 0
Psychiatric Disorders
Insomnia | 13 (16%) | 3 (7%)
Gastrointestinal Disorders
Abdominal pain | 9 (11%) | 0
Dyspepsia | 6 (7%) | 0
MedDRA version 9 is used.

Among 291 adult patients with ITP who received Nplate in the single-arm extension study, the incidence rates of the adverse reactions occurred in a pattern similar to those reported in the placebo-controlled clinical studies.

The safety profile of Nplate was similar across patients, regardless of ITP duration. The following adverse reactions (at least 5% incidence and at least 5% more frequent with Nplate compared with placebo or standard of care) occurred in Nplate patients with ITP duration up to 12 months: bronchitis, sinusitis, vomiting, arthralgia, myalgia, headache, dizziness, diarrhea, upper respiratory tract infection, cough, nausea and oropharyngeal pain. The adverse reaction of thrombocytosis occurred with an incidence of 2% in adults with ITP duration up to 12 months.

Bone Marrow Reticulin Formation and Collagen Fibrosis

Nplate administration may increase the risk for development or progression of reticulin fiber formation within the bone marrow. This formation may improve upon discontinuation of Nplate. In a clinical trial, one patient with ITP and hemolytic anemia developed marrow fibrosis with collagen during Nplate therapy.

An open-label clinical trial prospectively evaluated changes in bone marrow reticulin formation and collagen fibrosis in adult patients with ITP treated with Nplate or a non-US approved romiplostim product. Patients were administered romiplostim by SC injection once weekly for up to 3 years. Based on cohort assignment at time of study enrollment, patients were evaluated for bone marrow reticulin and collagen at year 1 (cohort 1), year 2 (cohort 2), or year 3 (cohort 3) in comparison to the baseline bone marrow at start of the trial. Patients were evaluated for bone marrow reticulin formation and collagen fibrosis using the modified Bauermeister grading scale. From the total of 169 patients enrolled in the 3 cohorts, 132 (78%) patients were evaluable for bone marrow collagen fibrosis and 131 (78%) patients were evaluable for bone marrow reticulin formation. Two percent (2/132) of patients (both from cohort 3) developed Grade 4 findings (presence of collagen). There was no detectable bone marrow collagen in one patient on repeat testing 12 weeks after discontinuation of romiplostim. Progression of bone marrow reticulin formation (increase greater than or equal to 2 grades or more) or an increase to Grade 4 (presence of collagen) was reported in 7% (9/131) of patients.

Pediatric Patients

The data described below reflect median exposure to Nplate of 168 days for 59 pediatric patients (aged 1 to 17 years) with ITP for at least 6 months, of whom 47.5% were female, across the randomized phase of two placebo-controlled trials. Table 4 presents the most common adverse reactions experienced by at least 5% of the pediatric patients (1 year and older) receiving Nplate across the two placebo-controlled trials with at least a 5% higher incidence in patients who received Nplate compared to those who received placebo.

Table 4. Common Adverse Reactions (≥ 5% Incidence and ≥ 5% More Frequent on the Nplate Arm) from Two Placebo-Controlled Trials in Pediatric Patients with ITP for at least 6 months
Adverse Reactions by Body System | Nplate (%) (N = 59) | Placebo (%) (N = 24)
Infections and Infestations
Upper Respiratory Tract Infection | 18 (31%) | 6 (25%)
Ear Infection | 3 (5%) | 0
Gastroenteritis | 3 (5%) | 0
Sinusitis | 3 (5%) | 0
Respiratory, Thoracic and Mediastinal Disorders
Oropharyngeal Pain | 15 (25%) | 1 (4%)
Gastrointestinal Disorders
Diarrhea | 12 (20%) | 3 (13%)
Abdominal Pain Upper | 8 (14%) | 1 (4%)
Skin and Subcutaneous Tissue Disorders
Rash | 9 (15%) | 2 (8%)
Purpura | 4 (7%) | 0
Urticaria | 3 (5%) | 0
General Disorders and Administration Site Conditions
Pyrexia | 14 (24%) | 2 (8%)
Peripheral Swelling | 4 (7%) | 0
Injury, Poisoning and Procedural Complications
Contusion | 24 (41%) | 8 (33%)
MedDRA version 20.1 is used.
In pediatric patients of age ≥ 1 year receiving Nplate for ITP, adverse reactions with an incidence of ≥ 25% in the two randomized trials were: contusion (41%), upper respiratory tract infection (31%), and oropharyngeal pain (25%).

Among 203 pediatric patients with ITP who received Nplate in a single arm, open-label, long-term (median duration of 3 years on therapy) study, the incidence rates of the adverse reactions occurred in a pattern similar to those reported in the placebo-controlled clinical studies. In this single arm, open-label, long-term study, headache occurred in 78 patients (38%), 3% (n=6) being severe and 1% (n=2) resulting in discontinuation of drug.

Bone Marrow Reticulin Formation and Collagen Fibrosis

The open-label long-term study also evaluated changes in bone marrow reticulin and collagen formation. The modified Bauermeister grading scale was used for both assessments. Based on cohort assignment at the time of study enrollment, patients were evaluated for bone marrow reticulin and collagen at year 1 (cohort 1) or year 2 (cohort 2) in comparison to the baseline bone marrow at the start of the study. From the total of 79 patients enrolled in the 2 cohorts, 27 (90%) patients in cohort 1 and 36 (73.5%) patients in cohort 2 had evaluable on-study bone marrow biopsies. Increased reticulin fiber formation was reported for 18.5% (5 of 27) of patients in cohort 1 and 47.2% (17 of 36) of patients in cohort 2, with a maximum grade of 2. No patients in either cohort developed collagen fibrosis (defined as grade 4) or a bone marrow abnormality that was inconsistent with an underlying diagnosis of ITP.

6.2 Postmarketing Experience

The following adverse reactions have been identified during post approval use of Nplate. Because these reactions are reported voluntarily from a population of uncertain size, it is not always possible to reliably estimate their frequency or establish a causal relationship to drug exposure.

- Erythromelalgia
- Hypersensitivity reactions including angioedema and anaphylaxis

6.3 Immunogenicity

As with all therapeutic proteins, there is a potential for immunogenicity. The detection of antibody formation is highly dependent on the sensitivity and specificity of the assay. Additionally, the observed incidence of antibody (including neutralizing antibody) positivity in an assay may be influenced by several factors including assay methodology, sample handling, timing of sample collection, concomitant medications, and underlying disease. For these reasons, comparison of the incidence of antibodies to Nplate in the studies described below with the incidence of antibodies in other studies or to other products may be misleading. Patients were screened for immunogenicity to romiplostim using a BIAcore-based biosensor immunoassay. This assay is capable of detecting both high- and low-affinity binding antibodies that bind to romiplostim and cross-react with TPO. The samples from patients that tested positive for binding antibodies were further evaluated for neutralizing capacity using a cell-based bioassay.

In adult clinical studies in adult patients with ITP, the incidence of pre-existing antibodies to romiplostim was 3.3% (35/1046) and the incidence of binding antibody development during treatment with Nplate or a non-US approved romiplostim product was 5.7% (60/1046). The incidence of pre-existing antibodies to endogenous TPO was 3% (31/1046) and the incidence of binding antibody development to endogenous TPO during treatment was 3.2% (33/1046). Of the patients with positive binding antibodies that developed to romiplostim or to TPO, four patients had neutralizing activity to romiplostim and none had neutralizing activity to TPO. No apparent correlation was observed between antibody activity and clinical effectiveness or safety.

In pediatric studies, data on antibody formation was collected from 282 patients (20 from early phase studies, 59 from phase 3 studies with duration of 6 months and 203 from a long-term study with median duration of 3 years). The incidence of binding antibodies to Nplate at any time was 9.6% (27/282), of which 2 patients (0.7%) had pre-existing binding non-neutralizing Nplate antibodies at baseline and 11 patients (3.9%) had persistent binding antibody positivity at end of study. Additionally, 2.8% (8/282) developed neutralizing antibodies to Nplate, with 4 patients (1.4%) having persistent neutralizing antibody positivity at end of study, despite discontinuation of Nplate. The incidence of binding antibodies to TPO at any time was 3.9% (11/282), of which 2 patients (0.7%) had pre-existing binding non-neutralizing antibodies to TPO at baseline and 1 patient (0.4%) had binding persistent antibody positivity at end of study. One patient (0.4%) had a weakly positive postbaseline result for neutralizing antibodies against TPO while on study (with positive non-neutralizing antibodies to Nplate) with a negative result at baseline for both antibodies. The patient showed a transient antibody response for neutralizing antibodies against TPO, with a negative result at the patient's last timepoint tested within the study period after discontinuation of Nplate.

A postmarketing registry study involving patients with thrombocytopenia on Nplate or a non-US approved romiplostim product was conducted to assess the long-term consequences of the anti-romiplostim antibodies. Adult patients who lacked response or lost response to Nplate or a non-US approved romiplostim product were enrolled. The incidence of new binding antibody development was 3.8% (7/184) to romiplostim and 2.2% (4/184) were positive for binding, non-neutralizing antibodies to TPO; two patients were positive for binding antibodies to both romiplostim and TPO. Of the seven patients with positive binding antibodies to romiplostim, one patient (0.5%; 1/184) was positive for neutralizing antibodies to romiplostim only.

Nineteen confirmed pediatric patients were included in the postmarketing registry study. The incidence of binding antibody post treatment was 16% (3/19) to romiplostim, of which 5.3% (1/19) were positive for neutralizing antibodies to romiplostim. There were no antibodies detected to TPO.

Immunogenicity assay results are highly dependent on the sensitivity and specificity of the assay used in detection and may be influenced by several factors, including sample handling, concomitant medications, and underlying disease. For these reasons, comparison of incidence of antibodies to romiplostim with the incidence of antibodies to other products may be misleading.

7 DRUG INTERACTIONS

Nplate may be used with other medical ITP therapies, such as corticosteroids, danazol, azathioprine, intravenous immunoglobulin (IVIG), and anti-D immunoglobulin [see Clinical Studies (14.1)].

8 USE IN SPECIFIC POPULATIONS

8.1 Pregnancy

Risk Summary

Based on findings from animal reproduction studies, Nplate may cause fetal harm when administered to a pregnant woman. Available data with Nplate use in pregnant women are insufficient to draw conclusions about any drug-associated risk for major birth defects, miscarriage, or adverse maternal or fetal outcomes. In animal reproduction and developmental toxicity studies, romiplostim crossed the placenta, and adverse fetal effects included thrombocytosis, postimplantation loss, and an increase in pup mortality (see Data).

The estimated background risk of major birth defects and miscarriage for the indicated population is unknown. All pregnancies have a background risk of birth defect, loss, or other adverse outcomes. In the U.S. general population, the estimated background risks of major birth defects and miscarriage in clinically recognized pregnancies is 2-4% and 15-20%, respectively.

Data

Animal Data

In rat and rabbit embryo-fetal development toxicity studies, no evidence of fetal harm was observed at romiplostim doses up to 11 times (rats) and 82 times (rabbits) the maximum human dose (MHD) based on systemic exposure (AUC). In mice at doses 5 times the MHD, reductions in maternal body weight and increased postimplantation loss occurred.

In a prenatal and postnatal development study in rats, at doses 11 times the MHD, there was an increase in perinatal pup mortality. Romiplostim crossed the placental barrier in rats and increased fetal platelet counts at clinically equivalent and higher doses.

8.2 Lactation

Risk Summary

There is no information regarding the presence of romiplostim in human milk, the effects on the breastfed child, or the effects on milk production. Maternal IgG is known to be present in human milk. The effects of local gastrointestinal exposure and limited systemic exposure in the breastfed child to romiplostim are unknown. Due to the potential for serious adverse reactions in a breastfed child from Nplate, advise women not to breastfeed during treatment with Nplate.

8.4 Pediatric Use

Safety and effectiveness of Nplate have been established in pediatric patients age 1 year and older with ITP for at least 6 months evaluated in two randomized, placebo-controlled studies. Long-term safety in the same population using Nplate for a median duration of 3 years was also evaluated in a single arm, open-label study [see Adverse Reactions (6.1), Clinical Studies (14.2)].

The pharmacokinetics of romiplostim have been evaluated in pediatric patients 1 year and older with ITP [see Clinical Pharmacology (12.3)]. See Dosage and Administration (2.1) for dosing recommendations for pediatric patients 1 year and older.

The safety and efficacy of Nplate in pediatric patients younger than 1 year with ITP have not been established. Serum concentrations of romiplostim in pediatric patients with ITP were within the range observed in adult patients with ITP receiving the same dose range of romiplostim.

The use of Nplate to increase survival in pediatric patients (including term neonates) acutely exposed to myelosuppressive doses of radiation is based on efficacy studies conducted in adult animals. Efficacy studies of Nplate could not be conducted in humans with acute radiation syndrome for ethical and feasibility reasons. A similar response to Nplate is expected in the pediatric and adult patients based on the mechanism of action of the drug and pharmacokinetics of Nplate in pediatric patients 1 year and older with ITP [see Dosage and Administration (2.2) and Clinical Pharmacology (12.3)].

8.5 Geriatric Use

Of the 271 patients who received Nplate in ITP clinical studies, 55 (20%) were age 65 and over, and 27 (10%) were 75 and over. No overall differences in safety or efficacy have been observed between older and younger patients in the placebo-controlled studies, but greater sensitivity of some older individuals cannot be ruled out. In general, dose adjustment for an elderly patient should be cautious, reflecting the greater frequency of decreased hepatic, renal, or cardiac function, and of concomitant disease or other drug therapy.

10 OVERDOSAGE

Overdoses due to medication errors have been reported in patients receiving Nplate. In the event of overdose, platelet counts may increase excessively and result in thrombotic/thromboembolic complications. In this case, discontinue Nplate and monitor platelet counts. Reinitiate treatment with Nplate in accordance with dosing and administration recommendations [see Dosage and Administration (2.1, 2.3)].

11 DESCRIPTION

Romiplostim is a thrombopoietin receptor agonist (TPO-RA). Romiplostim, a member of the TPO mimetic class, is an Fc-peptide fusion protein (peptibody). The peptibody molecule contains two identical single-chain subunits, each consisting of human immunoglobulin IgG1 Fc domain, covalently linked at the C-terminus to a peptide containing two thrombopoietin receptor-binding domains. Romiplostim has no amino acid sequence homology to endogenous TPO. Romiplostim is produced by recombinant DNA technology in Escherichia coli (E. coli).

Nplate (romiplostim) for injection is supplied as a sterile, preservative-free, lyophilized, solid white powder for subcutaneous use. Nplate is supplied as either 125 mcg per vial, 250 mcg per vial or 500 mcg per vial of romiplostim and requires reconstitution with Sterile Water for Injection to obtain a concentration of 500 mcg/mL.

Each single-dose 125 mcg vial of Nplate contains the following: 125 mcg of romiplostim, L-histidine (0.7 mg), mannitol (18 mg), polysorbate 20 (0.02 mg), sucrose (9 mg), and sufficient HCl to adjust the pH to a target of 5. Reconstitution with 0.44 mL of Sterile Water for Injection provides a resulting concentration of 125 mcg/0.25 mL.

Each single-dose 250 mcg vial of Nplate contains the following: 250 mcg romiplostim, L-histidine (1.2 mg), mannitol (30 mg), polysorbate 20 (0.03 mg), sucrose (15 mg), and sufficient HCl to adjust the pH to a target of 5. Reconstitution with 0.72 mL of Sterile Water for Injection provides a resulting concentration of 250 mcg/0.5 mL.

Each single-dose 500 mcg vial of Nplate contains the following: 500 mcg romiplostim, L-histidine (1.9 mg), mannitol (50 mg), polysorbate 20 (0.05 mg), sucrose (25 mg), and sufficient HCl to adjust the pH to a target of 5. Reconstitution with 1.2 mL of Sterile Water for Injection provides a resulting concentration of 500 mcg/mL.

12 CLINICAL PHARMACOLOGY

12.1 Mechanism of Action

Nplate increases platelet production through binding and activation of the TPO receptor, a mechanism analogous to endogenous TPO.

12.2 Pharmacodynamics

In clinical studies, treatment with Nplate resulted in dose-dependent increases in platelet counts. After a single subcutaneous dose of 1 to 10 mcg/kg Nplate in patients with ITP, the peak platelet count was 1.3 to 14.9 times greater than the baseline platelet count over a 2- to 3-week period. The platelet counts were above 50 × 10^9/L for seven out of eight patients with ITP who received six weekly doses of Nplate at 1 mcg/kg.

In a clinical study, peak platelet count increased 4.7 to 7.3 fold (mean: 5.8 fold) above baseline values in healthy adults (n = 4) administered a single 10 mcg/kg IV dose of Nplate.

Results from population modeling and simulation indicate that a single 10 mcg/kg subcutaneous dose of Nplate would result in clinically relevant effects on incidence rate and duration of severe thrombocytopenia in patients acutely exposed to myelosuppressive doses of radiation.

12.3 Pharmacokinetics

Patients with Immune Thrombocytopenia (ITP)

In the long-term extension study in adult patients with ITP receiving weekly treatment of Nplate subcutaneously, the pharmacokinetics of romiplostim over the dose range of 3 to 15 mcg/kg indicated that peak serum concentrations of romiplostim were observed about 7 to 50 hours post dose (median: 14 hours) with half-life values ranging from 1 to 34 days (median: 3.5 days). The serum concentrations varied among patients and did not correlate with the dose administered. The elimination of serum romiplostim is in part dependent on the TPO receptor on platelets. As a result, for a given dose, patients with high platelet counts are associated with low serum concentrations and vice versa. In another ITP clinical study, no accumulation in serum concentrations was observed (n = 4) after six weekly doses of Nplate (3 mcg/kg). The accumulation at higher doses of romiplostim is unknown.

Patients Acutely Exposed to Myelosuppressive Doses of Radiation

The pharmacokinetics of romiplostim is not available in patients acutely exposed to myelosuppressive doses of radiation.

Specific Populations

Pediatric Patients

Serum concentrations of romiplostim in pediatric patients with ITP were within the range observed in adult patients with ITP receiving the same dose range of romiplostim. Similar to adults with ITP, romiplostim pharmacokinetics are highly variable in pediatric patients with ITP.

13 NONCLINICAL TOXICOLOGY

13.1 Carcinogenesis, Mutagenesis, Impairment of Fertility

The carcinogenic potential of romiplostim has not been evaluated. The mutagenic potential of romiplostim has not been evaluated. Romiplostim had no effect on the fertility of rats at doses up to 37 times the MHD based on systemic exposure.

13.2 Animal Toxicology and/or Pharmacology

In a 4-week repeat-dose toxicity study in which rats were dosed subcutaneously three times per week, romiplostim caused extramedullary hematopoiesis, bone hyperostosis, and marrow fibrosis at clinically equivalent and higher doses. In this study, these findings were not observed in animals after a 4-week post treatment recovery period. Studies of long-term treatment with romiplostim in rats have not been conducted; therefore, it is not known if the fibrosis of the bone marrow is reversible in rats after long-term treatment.

14 CLINICAL STUDIES

14.1 Adults with ITP

The safety and efficacy of Nplate in adults with ITP were assessed in two double-blind, placebo-controlled clinical studies, an open-label single-arm study, and in an open-label extension study.

Studies 1 (NCT00102336) and 2 (NCT00102323)

In Studies 1 and 2, patients with ITP who had completed at least one prior treatment and had a platelet count of ≤ 30 × 10^9/L prior to study entry were randomized (2:1) to 24 weeks of Nplate (1 mcg/kg subcutaneous [SC]) or placebo. The median time since ITP diagnosis for Studies 1 and 2 was 2.1 years (range 0.1 to 31.6) and 8 years (range 0.6 to 44.8), respectively. Prior ITP treatments in both study groups included corticosteroids, immunoglobulins, rituximab, cytotoxic therapies, danazol, and azathioprine. Patients already receiving ITP medical therapies at a constant dosing schedule were allowed to continue receiving these medical treatments throughout the studies. Rescue therapies (i.e., corticosteroids, IVIG, platelet transfusions, and anti-D immunoglobulin) were permitted for bleeding, wet purpura, or if the patient was at immediate risk for hemorrhage. Patients received single weekly SC injections of Nplate, with individual dose adjustments to maintain platelet counts (50 × 10^9/L to 200 × 10^9/L).

Study 1 evaluated patients who had not undergone a splenectomy. The patients had been diagnosed with ITP for approximately 2 years and had received a median of three prior ITP treatments. Overall, the median platelet count was 19 × 10^9/L at study entry. During the study, the median weekly Nplate dose was 2 mcg/kg (25th–75th percentile: 1–3 mcg/kg).

Study 2 evaluated patients who had undergone a splenectomy. The patients had been diagnosed with ITP for approximately 8 years and had received a median of six prior ITP treatments. Overall, the median platelet count was 14 × 10^9/L at study entry. During the study, the median weekly Nplate dose was 3 mcg/kg (25th–75th percentile: 2–7 mcg/kg).

Study 1 and 2 outcomes are shown in Table 5. A durable platelet response was the achievement of a weekly platelet count ≥ 50 × 10^9/L for any 6 of the last 8 weeks of the 24-week treatment period in the absence of rescue medication at any time. A transient platelet response was the achievement of any weekly platelet counts ≥ 50 × 10^9/L for any 4 weeks during the treatment period without a durable platelet response. An overall platelet response was the achievement of either a durable or a transient platelet response. Platelet responses were excluded for 8 weeks after receiving rescue medications.

Table 5. Results from Placebo-Controlled Studies [All p values < 0.05 for platelet response and rescue therapy comparisons between Nplate and placebo.]
Outcomes | Study 1 Non-splenectomized Patients |  | Study 2 Splenectomized Patients
 | Nplate (n = 41) | Placebo (n = 21) | Nplate (n = 42) | Placebo (n = 21)
Platelet Responses and Rescue Therapy
Durable Platelet Response, n (%) | 25 (61%) | 1 (5%) | 16 (38%) | 0 (0%)
Overall Platelet Response, n (%) | 36 (88%) | 3 (14%) | 33 (79%) | 0 (0%)
Number of Weeks with Platelet Counts ≥ 50 × 10^9/L, average | 15 | 1 | 12 | 0
Requiring Rescue Therapy, n (%) | 8 (20%) | 13 (62%) | 11 (26%) | 12 (57%)
Reduction/Discontinuation of Baseline Concurrent ITP Medical Therapy
Receiving Therapy at Baseline | (n = 11) | (n = 10) | (n = 12) | (n = 6)
Patients Who Had > 25% Dose Reduction in Concurrent Therapy, n (%) | 4/11 (36%) | 2/10 (20%) | 4/12 (33%) | 1/6 (17%)
Patients Who Discontinued Baseline Therapy, n (%) [For multiple concomitant baseline therapies, all therapies were discontinued.] | 4/11 (36%) | 3/10 (30%) | 8/12 (67%) | 0/6 (0%)

In Studies 1 and 2, nine patients reported a serious bleeding event [five (6%) Nplate, four (10%) placebo]. Bleeding events that were Grade 2 severity or higher occurred in 15% of patients treated with Nplate and 34% of patients treated with placebo.

Study 3 (NCT01143038)

Study 3 was a single-arm, open-label study designed to assess the safety and efficacy of Nplate in adult patients who had an insufficient response (platelet count ≤ 30 x 10^9/L) to first-line therapy. The study enrolled 75 patients of whom the median age was 39 years (range 19 to 85) and 59% were female.

The median time from ITP diagnosis to study enrollment was 2.2 months (range 0.1 to 6.6). Sixty percent of patients had ITP duration < 3 months and 40% had ITP duration ≥ 3 months. The median platelet count at screening was 20 x 10^9/L. Prior ITP treatments included corticosteroids, immunoglobulins and anti-D immunoglobulins. Patients already receiving ITP medical therapies at a constant dosing schedule were allowed to continue receiving these medical treatments throughout the studies. Rescue therapies (i.e., corticosteroids, IVIG, platelet transfusions, anti-D immunoglobulin, dapsone, danazol, and azathioprine) were permitted.

Patients received single weekly SC injections of Nplate over a 12-month treatment period, with individual dose adjustments to maintain platelet counts (50 x 10^9/L to 200 x 10^9/L). During the study, the median weekly Nplate dose was 3 mcg/kg (25th-75th percentile: 2-4 mcg/kg).

Of the 75 patients enrolled in Study 3, 70 (93%) had a platelet response ≥ 50 x 10^9/L during the 12-month treatment period. The mean number of months with platelet response during the 12-month treatment period was 9.2 (95% CI: 8.3, 10.1) months; the median was 11 (95% CI: 10, 11) months. The Kaplan-Meier estimate of the median time to first platelet response was 2.1 weeks (95% CI: 1.1, 3.0). Twenty-four (32%) patients maintained every platelet count ≥ 50 x 10^9/L for at least 6 months in the absence of Nplate and any medication for ITP (concomitant or rescue); the median time to onset of maintaining every platelet count ≥ 50 x 10^9/L for at least 6 months was 27 weeks (range 6 to 57).

Study 4 (NCT00116688) Extension Study

Patients who had completed a prior Nplate study (including Study 1 and Study 2) were allowed to enroll in a long-term open-label extension study. Following Nplate discontinuation in Studies 1 and 2, seven patients maintained platelet counts of ≥ 50 × 10^9/L. Among 291 patients who subsequently entered the extension study and received Nplate, platelet counts were increased and sustained regardless of whether they had received Nplate or placebo in the prior placebo-controlled studies. The majority of patients reached a median platelet count of 50 × 10^9/L after receiving one to three doses of Nplate, and these platelet counts were maintained throughout the remainder of the study with a median duration of Nplate treatment of 78 weeks and a maximum duration of 277 weeks.

14.2 Pediatric Patients with ITP

The safety and efficacy of Nplate in pediatric patients 1 year and older with ITP for at least 6 months were assessed in two double-blind, placebo-controlled clinical trials.

Study 5 (NCT01444417)

In Study 5, patients refractory or relapsed after at least one prior ITP therapy with a platelet count ≤ 30 x 10^9/L were stratified by age and randomized (2:1) to receive Nplate (n = 42) or placebo (n = 20). The starting dose for all ages was 1 mcg/kg weekly. Over a 24-week treatment period, dose was titrated up to a maximum of 10 mcg/kg weekly of either Nplate or placebo in an effort to maintain a target platelet count of ≥ 50 × 10^9/L to 200 × 10^9/L.

The median age of the patients was 9.5 years (range 3 to 17) and 57% were female. Approximately 58% of patients had a baseline count ≤ 20 x 10^9/L, which was similar between treatment arms. The percentage of patients with at least 2 prior ITP therapies (predominantly immunoglobulins and corticosteroids) was 81% in the group treated with Nplate and 70% in the group treated with placebo. One patient in each group had undergone splenectomy.

Study 5 results are shown in Table 6. The efficacy of Nplate in this trial was measured by the proportion of patients receiving Nplate achieving a durable platelet response and the proportion of patient achieving an overall platelet response. A durable platelet response was defined as achieving at least 6 weekly platelet counts ≥ 50 × 10^9/L during weeks 18 through 25 of treatment. A transient platelet response was defined as a weekly platelet count ≥ 50 × 10^9/L for 4 or more times during weeks 2 through 25, but without durable platelet response. An overall platelet response was defined as a durable or a transient platelet response. Platelet responses were excluded for 4 weeks after receiving rescue medications.

Table 6. Results from Pediatric Placebo-Controlled Studies [All p values < 0.05 for platelet response between Nplate and placebo.]
Outcomes | Study 5
 | Nplate (n = 42) | Placebo (n = 20)
Platelet Responses and Rescue Therapy
Durable Platelet Response, n (%) | 22 (52%) | 2 (10%)
Overall Platelet Response, n (%) | 30 (71%) | 4 (20%)
Number of Weeks with Platelet Counts ≥ 50 x 10^9/L, median | 12 | 1

Study 6 (NCT00515203)

In study 6, patients diagnosed with ITP at least 6 months prior to enrollment with a platelet count ≤ 30 x 10^9/L were stratified by age and randomized (3:1) to receive Nplate (n = 17) or placebo (n = 5). The starting dose for all ages was 1 mcg/kg weekly. Over a 12-week treatment period dose was titrated up to a maximum of 10 mcg/kg weekly of either Nplate or placebo in an effort to maintain a target platelet count of ≥ 50 × 10^9/L to 250 × 10^9/L.

The median age of the patients was 10 years (range 1 to 17 years) and 27.3% of patients were female. Approximately 82% of patients had a baseline count ≤ 20 x 10^9/L, which was similar between treatment arms. The percentage of patients with at least 2 prior ITP therapies (predominantly IVIG and corticosteroids) was 88% in the group treated with Nplate and 100% in the group treated with placebo. Six patients in the Nplate group and 2 patients in the placebo group had undergone splenectomy.

The efficacy of Nplate in this trial was measured by the proportion of patients who achieved a platelet count of ≥ 50 × 10^9/L for 2 consecutive weeks and by the proportion of patients who achieved an increase in platelet count of ≥ 20 × 10^9/L above baseline for 2 consecutive weeks. Platelet responses within 4 weeks following rescue medications use were excluded. Of the 17 patients who received Nplate, 15 achieved a platelet count of ≥ 50 × 10^9/L for 2 consecutive weeks (88.2%, 95% CI: 63.6%, 98.5%).

The same 15 patients also achieved an increase in platelet count of ≥ 20 × 10^9/L above baseline for 2 consecutive weeks during the treatment period (88.2%, 95% CI: 63.6%, 98.5%). None of the patients treated with placebo achieved either endpoint.

Study 7 (NCT02279173) Long-Term Pediatric Study

In study 7, patients diagnosed with ITP at least 6 months prior to enrollment and who received at least 1 prior ITP therapy or were ineligible for other ITP therapies were enrolled to a study to evaluate efficacy for up to 3 years. Nplate was administered weekly for up to 3 years by subcutaneous injection starting at a dose of 1 mcg/kg with weekly increments to a maximum dose of 10 mcg/kg to reach a target platelet count between 50 × 10^9/L and 200 × 10^9/L. The median age of the patients was 10 years (range 1 to 17 years) and the median and maximum duration of treatment were 156 weeks and 163 weeks, respectively. Among the 203 patients, the mean (SD) and median percentage of time with a platelet response (platelet count ≥ 50 × 10^9/L) within the first 6 months of initiation of Nplate without rescue medication use for the past 4 weeks was 50.6% (37) and 50.0%, respectively. Sixty (29.6%) subjects overall received rescue medications. Rescue medications (i.e., corticosteroids, platelet transfusions, IVIG, azathioprine, anti-D immunoglobulin, and danazol) were permitted.

Figure 1. Summary of Efficacy Endpoints for Long-term Use of NPLATE (Study 7) - With Number of Patients With Bleeding Events, Number of Subjects With Rescue Medication Use, Number of Subjects on Treatment, Median Platelet Counts During the Treatment Period

The safety analysis set includes all subjects who received at least one dose of Nplate in study 7.
Bleeding events were identified using narrow search of pre-defined list of preferred terms for Haemorrhages (SMQ).
Incidence rate of bleeding event is calculated as the number of subjects with bleeding events/the number of subjects on treatment.
Incidence of rescue medication is calculated as the number of subjects with rescue medication/the number of subjects on treatment. Rescue medication start from week 1.
Only platelet counts where rescue medication was not administered less than 28 days prior to evaluation are included.

14.3 Patients with Hematopoietic Syndrome of Acute Radiation Syndrome

Efficacy studies of Nplate could not be conducted in humans with acute radiation syndrome for ethical and feasibility reasons. Approval for this indication was based on efficacy studies conducted in animals, Nplate's effect on platelet count in healthy human volunteers and on data supporting Nplate's effect on thrombocytopenia in patients with ITP and insufficient response to corticosteroids, immunoglobulins, or splenectomy.

Because of the uncertainty associated with extrapolating animal efficacy data to humans, the selection of a human dose for Nplate is aimed at providing platelet response to Nplate that is similar to that observed in efficacy studies conducted in animals. The recommended dose of Nplate for patients exposed to myelosuppressive doses of radiation is 10 mcg/kg administered once as a subcutaneous injection [see Dosage and Administration (2.2)]. The 10 mcg/kg dosing regimen for humans is based on population modeling and simulation analyses. For pediatric patients (including term neonates), extrapolation was based on data supporting Nplate's effect on thrombocytopenia in patients with ITP and an insufficient response to corticosteroids, immunoglobulins, or splenectomy.

The safety of Nplate for the acute radiation syndrome setting was assessed based on the clinical experience in patients with ITP [see Adverse Reactions (6)] and from a study with healthy volunteers. The efficacy of Nplate was studied in a randomized, blinded, placebo-controlled study in a non-human primate model of radiation injury. Rhesus monkeys were randomized to either a control (n = 40) or treated (n = 40) cohort. Animals were exposed to total body irradiation (TBI) of 6.8 Gy from a Cobalt^60 gamma ray source, representing a dose that would be lethal in 70% of animals by 60 days of follow-up (LD70/60). Animals were administered a single subcutaneous dose of blinded treatment (control article [sterile saline] or Nplate [5mg/kg]) 24 hours post-irradiation. The primary efficacy endpoint was survival. Animals received medical management consisting of intravenous or subcutaneous fluids, anti-ulcer medication, anti-emetic medication, analgesics, antimicrobials, and other support as required.

Nplate significantly (one-sided p = 0.0002) increased 60-day survival in the irradiated animals: 72.5% survival (29/40) in the Nplate group compared to 32.5% survival (13/40) in the control group. In the same study, an exploratory cohort of n=40 animals received Nplate (5mg/kg) on day 1 and pegfilgrastim (0.3mg/kg) on days 1 and 8 post-irradiation. Survival in this combined treatment group was 87.5% (95% CI: (73.2%, 95.8%)).

16 HOW SUPPLIED/STORAGE AND HANDLING

Nplate (romiplostim) for injection is supplied as a sterile, preservative-free, solid white lyophilized powder in single-dose vials of 125 mcg (NDC-55513-223-01, NDC-55513-223-21), 250 mcg (NDC 55513-221-01, NDC 55513-221-21) and 500 mcg (NDC 55513-222-01, NDC 55513-222-21) of romiplostim.

Store Nplate vials in the refrigerator at 2°C to 8°C (36°F to 46°F) in the original carton to protect from light. Do not freeze.

If needed, unopened Nplate vials may be stored in the original carton at room temperature up to a maximum of 25°C (77°F) for a single period of up to 30 days. The new expiration date must be written in the space provided on the carton. Once stored at room temperature, do not place back in the refrigerator. If not used within the 30 days, discard Nplate.

17 PATIENT COUNSELING INFORMATION

Advise the patient to read the FDA-approved patient labeling (Medication Guide).

Advise patients acutely exposed to myelosuppressive doses of radiation (Hematopoietic Syndrome of Acute Radiation Syndrome) that efficacy studies of Nplate for this indication could not be conducted in humans for ethical and feasibility reasons and that, therefore, approval of this use was based on efficacy studies conducted in animals [see Clinical Studies (14.3)].

Inform patients of the following risks and considerations for Nplate:

- Nplate therapy is administered to achieve and maintain a platelet count ≥ 50 × 10^9/L as necessary to reduce the risk for bleeding; Nplate is not used to normalize platelet counts.
- Following discontinuation of Nplate, thrombocytopenia and risk of bleeding may develop that is worse than that experienced prior to the Nplate therapy.
- Nplate therapy may increase the risk of reticulin fiber formation within the bone marrow. This formation may improve upon discontinuation. Detection of peripheral blood cell abnormalities may necessitate a bone marrow examination.
- Too much Nplate may result in excessive platelet counts and a risk for thrombotic/thromboembolic complications.
- Nplate stimulates certain bone marrow cells to make platelets and increases the risk of progression to acute myelogenous leukemia in patients with myelodysplastic syndromes.
- Platelet counts and CBCs must be performed weekly until a stable Nplate dose has been achieved; thereafter, platelet counts and CBCs must be performed monthly while taking Nplate.
- Patients must be closely monitored with weekly platelet counts and CBCs for at least 2 weeks following Nplate discontinuation.
- Even with Nplate therapy, patients should continue to avoid situations or medications that may increase the risk for bleeding.

Pregnancy:

- Advise pregnant women of the potential risk to a fetus. Advise females of reproductive potential to inform their prescriber of a known or suspected pregnancy [see Use in Specific Populations (8.1)].

Lactation:

- Advise women not to breastfeed during treatment with Nplate [see Use in Specific Populations (8.2)].

Nplate® (romiplostim)

Manufactured by:
Amgen Inc.
One Amgen Center Drive
Thousand Oaks, California 91320-1799
U.S. License No. 1080

Patent: http://pat.amgen.com/nplate/

© 2008-2025 Amgen Inc. All rights reserved.

www.nplate.com

1xxxxx

V21

MEDICATION GUIDE
Nplate® (N-plāt)
(romiplostim)
for injection

What is the most important information I should know about Nplate?
Nplate can cause serious side effects, including:

- Worsening of a precancerous blood condition to a blood cancer (leukemia). Nplate is not for use in people with a precancerous condition called myelodysplastic syndromes (MDS), or for any condition other than immune thrombocytopenia (ITP). If you have MDS and receive Nplate, your MDS condition may worsen and become an acute leukemia. If MDS worsens to become acute leukemia you may die sooner from the acute leukemia.
- Higher risk for blood clots.
  - You may have a higher risk of getting a blood clot if your platelet count becomes high during treatment with Nplate. Blood clots in the veins of your legs (deep vein thrombosis, DVT), lungs (pulmonary embolism, PE), heart attack and strokes have happened in people with ITP during treatment with Nplate.
  - You may get blood clots in the veins of your liver (portal vein thrombosis) with or without chronic liver disease. This may affect your liver function.

- Injection of too much Nplate may cause a dangerous increase in your blood platelet count and serious side effects. Your healthcare provider may change your dose or stop Nplate depending upon the change in your blood platelet count. You must have blood platelet counts done before you start, during, and after Nplate therapy is stopped (see “How will I receive Nplate?”).

See “What are the possible side effects of Nplate?” for other side effects of Nplate.

What is Nplate?

- Nplate is a prescription medicine used to treat low blood platelet counts (thrombocytopenia) in:
  - adults with immune thrombocytopenia (ITP) when certain medicines or surgery to remove your spleen have not worked well enough.
  - children 1 year of age and older with ITP for at least 6 months when certain medicines or surgery to remove your spleen have not worked well enough.
- Nplate is a prescription medicine also used to treat people including newborns who have been exposed to high levels of radiation (acute radiation syndrome). The effectiveness of Nplate for this use was only studied in animals, because it could not be studied in people.
- Nplate is not for use in people with a precancerous condition called myelodysplastic syndrome (MDS), or low platelet count caused by any condition other than ITP.
- Nplate is only used if your low platelet count and medical condition increase your risk of bleeding.
- Nplate is used to try to keep your platelet count about 50,000 per microliter in order to lower the risk for bleeding. Nplate is not used to make your platelet count normal.
- It is not known if Nplate is safe and effective in children under the age of 1.

Before receiving Nplate, first speak to your healthcare provider and understand the benefits and risks of Nplate. Be sure to tell your healthcare provider about all of your medical conditions, including if you:

- have had surgery to remove your spleen (splenectomy)
- have a bone marrow problem, including a blood cancer or MDS
- have or had a blood clot
- have chronic liver disease.
- have bleeding problems
- are pregnant or plan to become pregnant. Nplate may harm your unborn baby. Tell your healthcare provider if you become pregnant or think you may be pregnant during treatment with Nplate.
- are breastfeeding or plan to breastfeed. Nplate may pass into your breast milk and harm your baby. Do not breastfeed during treatment with Nplate.

Tell your healthcare provider about all the medicines you take, including prescription and over-the-counter medicines, vitamins, and herbal products.
Know the medicines you take. Keep a list of them and show it to your healthcare provider or pharmacist when you get a new medicine.

How will I receive Nplate?

- Nplate for ITP is given by your healthcare provider as an injection under the skin (subcutaneous) one time each week.
- Nplate is given by your healthcare provider as an injection under the skin once for exposure to high levels of radiation.
- During treatment for ITP, your healthcare provider will closely monitor your Nplate dose and platelet counts.
  ○ Your healthcare provider will check your platelet count every week and change your dose of Nplate as needed. This will continue until your healthcare provider decides that your dose of Nplate can stay the same. After that, you will need to get blood tests every month. When you stop receiving Nplate, you will need blood tests for at least 2 weeks to check if your platelet count drops too low.
  ○ Tell your healthcare provider about any bruising or bleeding that occurs during treatment with Nplate.
- If you miss a scheduled dose of Nplate, call your healthcare provider to schedule your next dose as soon as possible.

What should I avoid while receiving Nplate?
Avoid situations or medicines that may increase your risk of bleeding.

What are the possible side effects of Nplate?
Nplate may cause serious side effects. See “What is the most important information I should know about Nplate?”
The most common side effects of Nplate in adults include:

• headache

• tingling or numbness in hands and feet

• joint pain

• bronchitis

• dizziness

• inflammation of the sinuses (sinusitis)

• trouble sleeping

• vomiting

• muscle tenderness or weakness
• pain in the arms and legs
• stomach (abdomen) pain
• shoulder pain
• indigestion

• diarrhea
• upper respiratory tract infection
• cough
• nausea
• pain in mouth and throat (oropharyngeal pain)

The most common side effects of Nplate in children 1 year of age and older include:

• bruising
• upper respiratory tract infection

• pain in mouth and throat (oropharyngeal pain)

People who take Nplate may have an increased risk of developing new or worsening changes in the bone marrow called “increased reticulin”. These changes may improve if you stop taking Nplate. Your healthcare provider may need to check your bone marrow for this problem during treatment with Nplate.
These are not all of the possible side effects of Nplate. Call your doctor for medical advice about side effects. You may report side effects to FDA at 1-800-FDA-1088.
You may also report side effects to Amgen at 1-800-77-AMGEN (1-800-772-6436).

General information about the safe and effective use of Nplate.
Medicines are sometimes prescribed for purposes other than those listed in a Medication Guide. You can ask your pharmacist or healthcare provider for information about Nplate that is written for health professionals.

What are the ingredients in Nplate?
Active ingredient: romiplostim
Inactive ingredients: L-histidine, mannitol, polysorbate 20, sucrose, and hydrochloric acid
Nplate® (romiplostim)
Manufactured by: Amgen Inc., One Amgen Center Drive, Thousand Oaks, California 91320-1799
US License No. 1080.
Patent: http://pat.amgen.com/nplate/
© 2008-2025 Amgen Inc. All rights reserved. For more information go to www.nplate.com.
1xxxxxx v11

This Medication Guide has been approved by the U.S. Food and Drug Administration. Revised: 03/2025

PRINCIPAL DISPLAY PANEL - 500 mcg Vial Carton

1 Single Dose Vial

Rx Only
NDC 55513-222-01

AMGEN®

Nplate®
(romiplostim) For Injection

500
mcg/vial

500 mcg/vial
Reconstitute with 1.2 mL Sterile Water
for Injection, USP for a concentration of
500 mcg/1 mL.
For Subcutaneous Use Only
Single Dose Vial; Discard unused portion
Dispense the enclosed Medication
Guide to each patient.
Protect from light. Do not freeze.
DO NOT SHAKE reconstituted solution

PRINCIPAL DISPLAY PANEL - 125 mcg Vial Carton

1 Single Dose Vial

Rx Only
NDC 55513-223-01

AMGEN®

Nplate®
(romiplostim) For Injection

125
mcg/vial

125 mcg/vial
Reconstitute with 0.44 mL Sterile Water
for Injection, USP for a concentration of
125 mcg/0.25 mL.
For Subcutaneous Use Only
Single Dose Vial; Discard unused portion
Dispense the enclosed Medication
Guide to each patient.
Protect from light. Do not freeze.
DO NOT SHAKE reconstituted solution

PRINCIPAL DISPLAY PANEL - 250 mcg Vial Carton

1 Single Dose Vial

Rx Only
NDC 55513-221-01

AMGEN®

Nplate®
(romiplostim) For Injection

250
mcg/vial

250 mcg/vial
Reconstitute with 0.72 mL Sterile Water
for Injection, USP for a concentration of
250 mcg/0.5 mL.
For Subcutaneous Use Only
Single Dose Vial; Discard unused portion
Dispense the enclosed Medication
Guide to each patient.
Protect from light. Do not freeze.
DO NOT SHAKE reconstituted solution